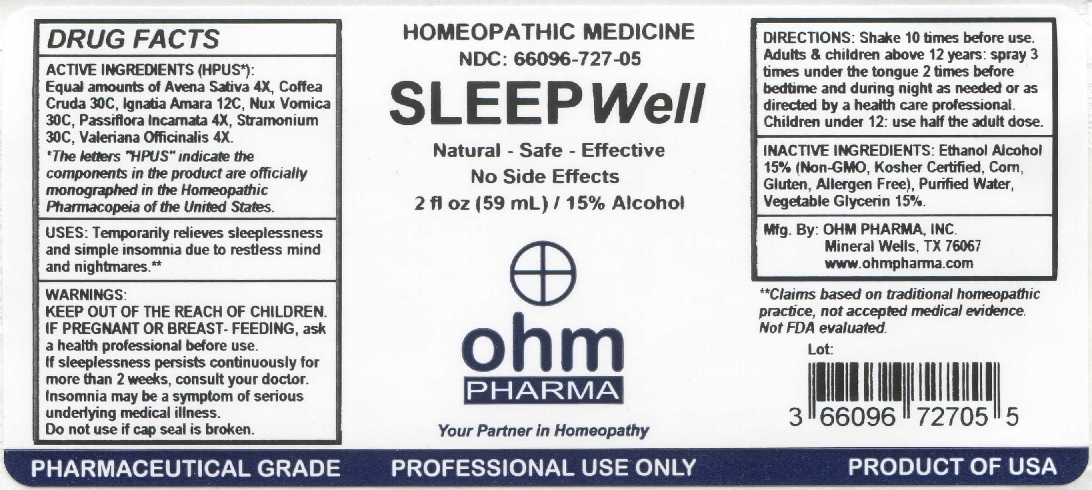 DRUG LABEL: OHM Sleep Well
NDC: 66096-727 | Form: LIQUID
Manufacturer: OHM PHARMA INC.
Category: homeopathic | Type: HUMAN OTC DRUG LABEL
Date: 20211229

ACTIVE INGREDIENTS: AVENA SATIVA FLOWERING TOP 4 [hp_X]/59 mL; ARABICA COFFEE BEAN 30 [hp_C]/59 mL; STRYCHNOS IGNATII SEED 12 [hp_C]/59 mL; STRYCHNOS NUX-VOMICA SEED 30 [hp_C]/59 mL; PASSIFLORA INCARNATA FLOWERING TOP 4 [hp_X]/59 mL; DATURA STRAMONIUM 30 [hp_C]/59 mL; VALERIAN 4 [hp_X]/59 mL
INACTIVE INGREDIENTS: ALCOHOL; WATER; GLYCERIN

OHM Sleep Well

ACTIVE INGREDIENT

ACTIVE INGREDIENTS (HPUS*): Equal amounts of: Avena Sativa 4X, Coffea Cruda 30C, Ignatia Amara 12C, Nux Vomica 30C, Passiflora Incarnata 4X, Stramonium 30C, Valeriana Officinalis 4X.

*The letters "HPUS" indicate that the components in this product are officially monographed in the Homeopathic Pharmacopeia of the United States.

INDICATIONS AND USAGE

USES: Temporarily relieves sleeplessness and simple insomnia due to restless mind and nightmares.**

**Claims based on traditional homeopathic practice, not accepted medical evidence. Not FDA evaluated.

WARNINGS

WARNINGS: IF PREGNANT OR BREAST-FEEDING, ask a health professional before use. If sleeplessness persists continuously for more than 2 weeks, consult your doctor. Insomnia may be a symptom of serious underlying medical illness.

- KEEP OUT OF REACH OF CHILDREN.

DOSAGE AND ADMINISTRATION

DIRECTIONS: Shake 10 times before use. Adults & children above 12 years: spray 3 times under the tongue 2 times before bedtime and during night as needed or as directed by a health care professional. Children under 12: use half the adult dose.

Do not use if cap seal is broken.

INACTIVE INGREDIENT

INACTIVE INGREDIENTS: Ethanol Alcohol 15% (Non-GMO, Kosher Certified, Corn, Gluten, Allergen Free), Purified Water, Vegetable Glycerin 15%

QUESTIONS

Mfg. By: OHM PHARMA, INC. Mineral Wells, TX 76067

www.ohmpharma.com

PACKAGE LABEL

HOMEOPATHIC MEDICINE

NDC: 66096-727-05

SLEEP Well

Natural - Safe - Effective

No Side Effects

2 fl oz (59mL) / 15% Alcohol

PRODUCT OF USA

PURPOSE

Insomnia